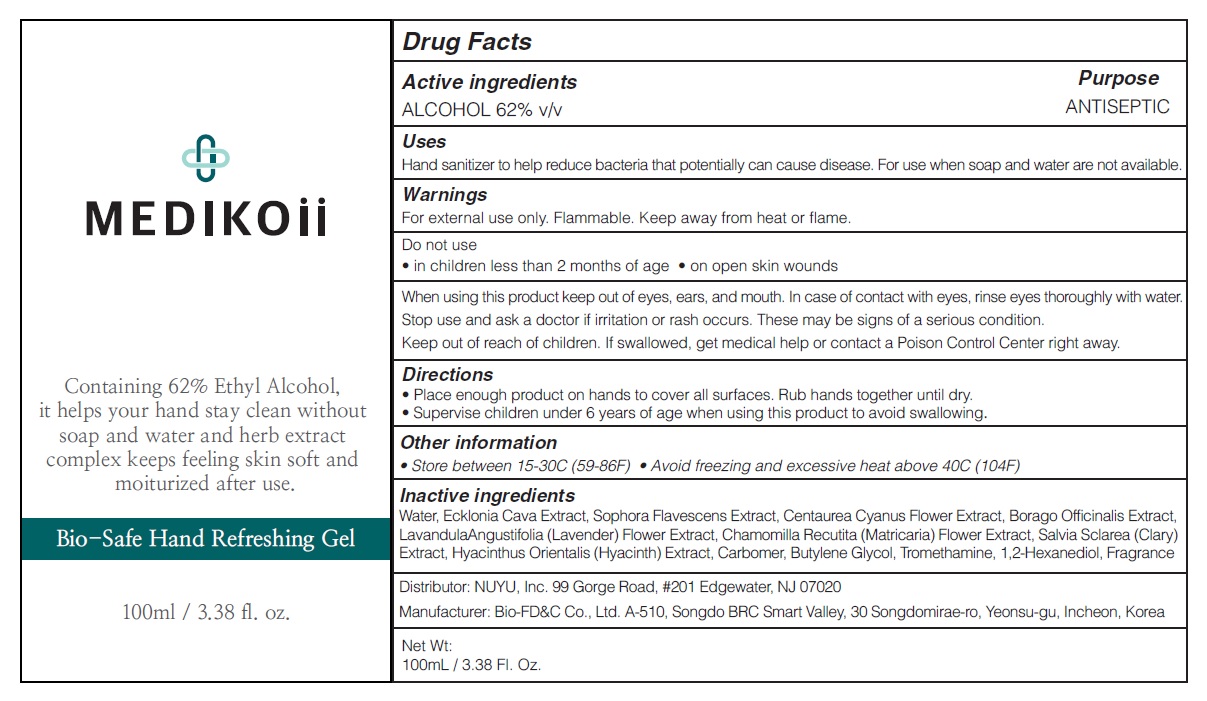 DRUG LABEL: MEDIKOii Bio Safe Hand Refreshing
NDC: 72695-0014 | Form: GEL
Manufacturer: THERANOTICS CO.,LTD.
Category: otc | Type: HUMAN OTC DRUG LABEL
Date: 20200615

ACTIVE INGREDIENTS: ALCOHOL 62 mL/100 mL
INACTIVE INGREDIENTS: Water; ECKLONIA CAVA; SOPHORA FLAVESCENS ROOT; CENTAUREA CYANUS FLOWER; BORAGO OFFICINALIS SEED; LAVANDULA ANGUSTIFOLIA SUBSP. ANGUSTIFOLIA FLOWER; CHAMOMILE; CARBOMER HOMOPOLYMER, UNSPECIFIED TYPE; Butylene Glycol; TROLAMINE; 1,2-Hexanediol

Drug Facts

ACTIVE INGREDIENTS

ALCOHOL 62% v/v

INACTIVE INGREDIENTS

Water, Ecklonia Cava Extract, Sophora Flavescens Extract, Centaurea Cyanus Flower Extract, Borago Officinalis Extract, Lavandula Angustifolia (Lavender) Flower Extract, Chamomilla Recutita (Matricaria) Flower Extract, Salvia Sclarea (Clary) Extract, Hyacinthus Orientalis (Hyacinth) Extract, Carbomer, Butylene Glycol, Tromethamine, 1,2-Hexanediol, Fragrance

PURPOSE

ANTISEPTIC

WARNINGS

For external use only. Flammable. Keep away from heat or flame
--------------------------------------------------------------------------------------------------------
Do not use
• in children less than 2 months of age
• on open skin wounds
--------------------------------------------------------------------------------------------------------
When using this product keep out of eyes, ears, and mouth. In case of contact with eyes, rinse eyes thoroughly with water.
--------------------------------------------------------------------------------------------------------
Stop use and ask a doctor if irritation or rash occurs. These may be signs of a serious condition.

KEEP OUT OF REACH OF CHILDREN

If swallowed, get medical help or contact a Poison Control Center right away.

Uses

Hand sanitizer to help reduce bacteria that potentially can cause disease. For use when soap and water are not available.

Directions

• Place enough product on hands to cover all surfaces. Rub hands together until dry.
• Supervise children under 6 years of age when using this product to avoid swallowing.

Other information

• Store between 15-30C (59-86F)
• Avoid freezing and excessive heat above 40C (104F)